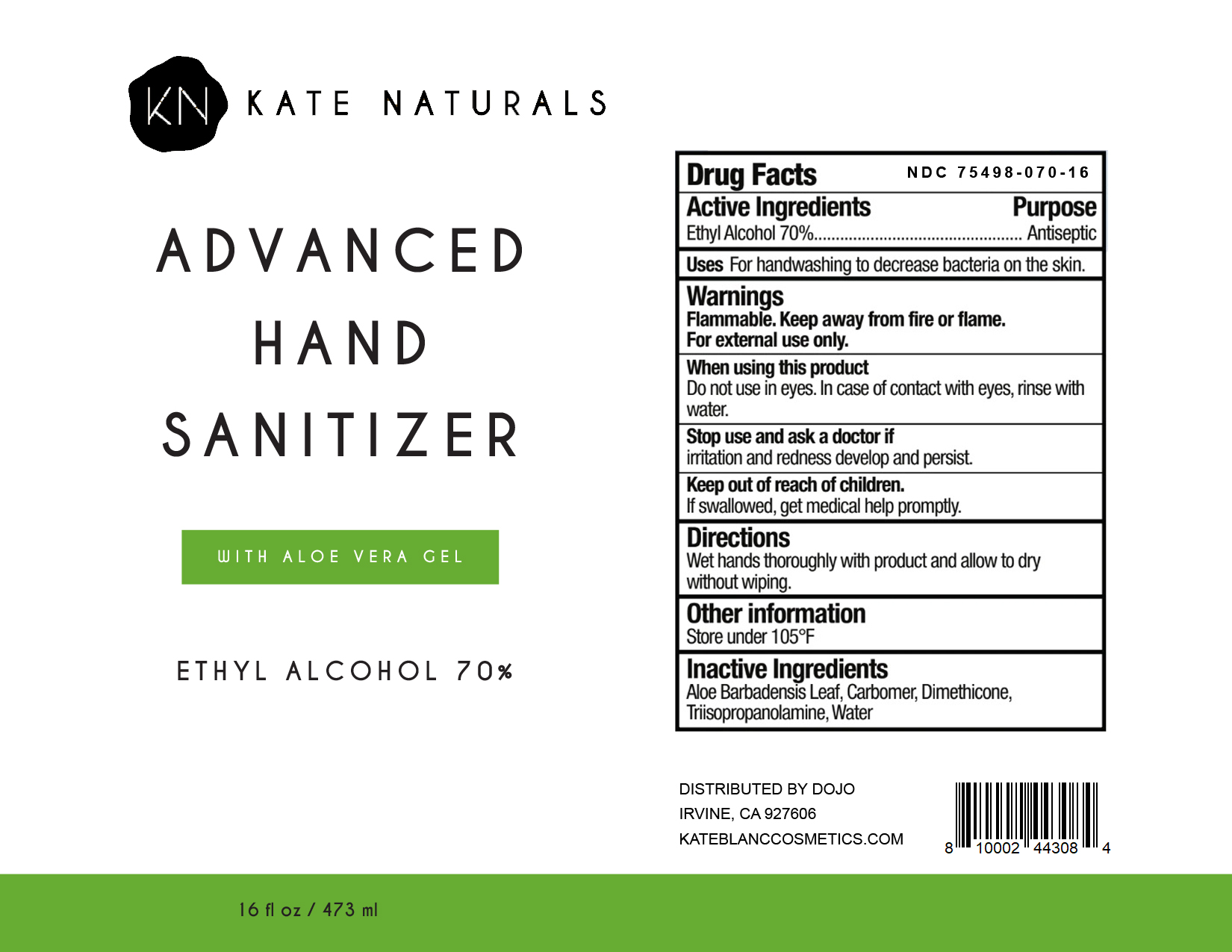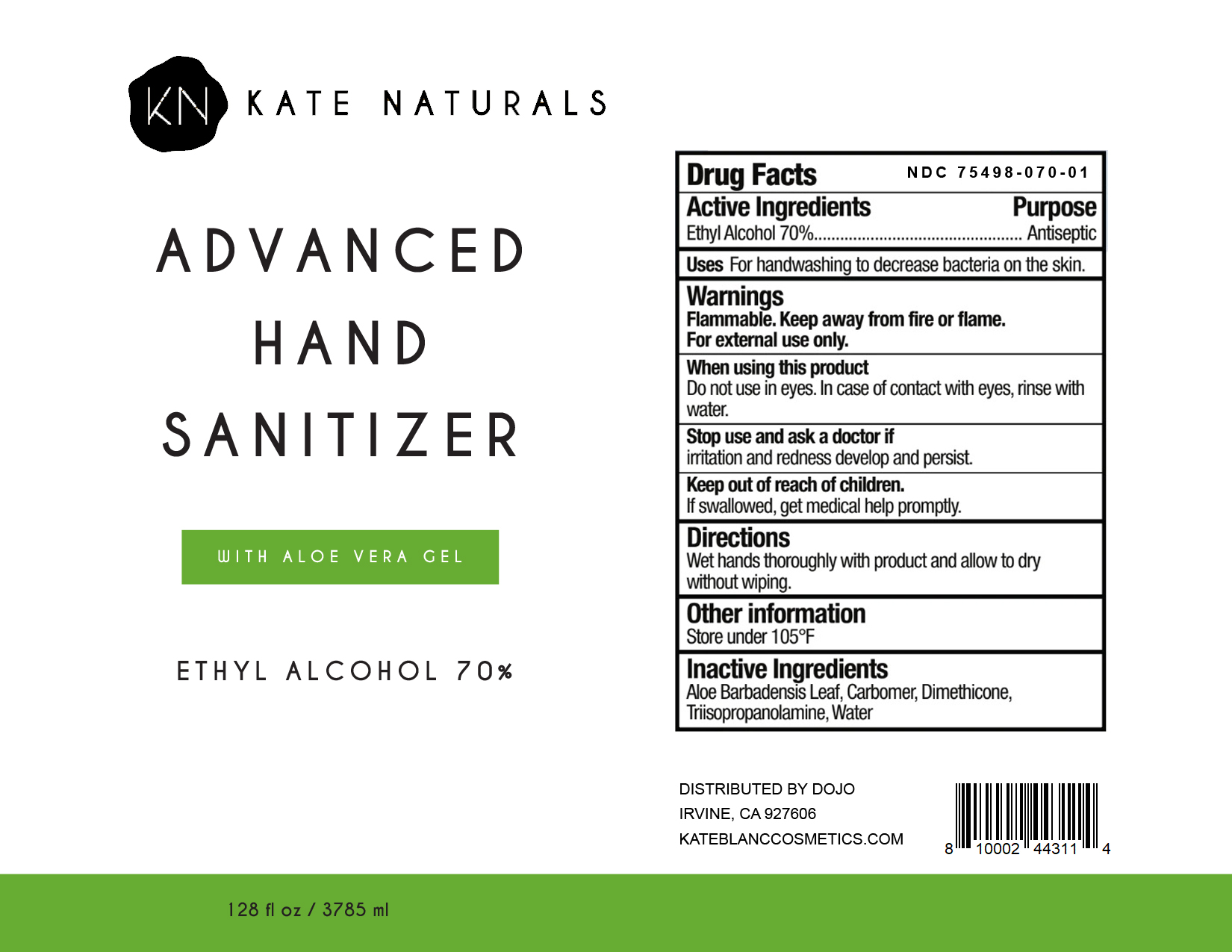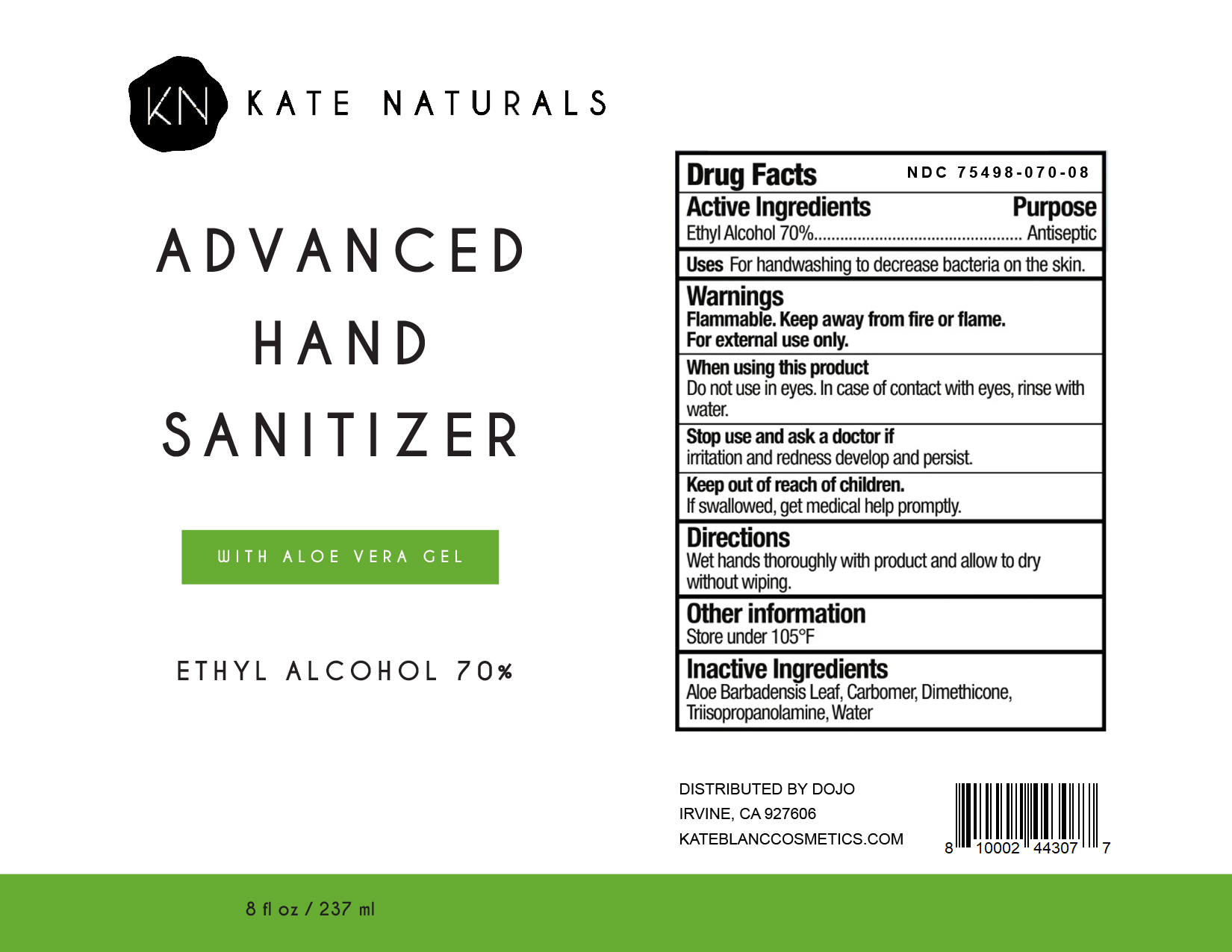 DRUG LABEL: Kate Naturals Advanced Hand Sanitizer
NDC: 75498-070 | Form: GEL
Manufacturer: THE DOJO LLC
Category: otc | Type: HUMAN OTC DRUG LABEL
Date: 20200415

ACTIVE INGREDIENTS: ISOPROPYL ALCOHOL 70 mL/100 mL
INACTIVE INGREDIENTS: ALOE VERA LEAF; CARBOMER 940; WATER; DIMETHICONE 100; FENOPROP TRIISOPROPANOLAMINE

This hand sanitizer is manufactured using the following ingredients:

1. Ethyl Alcohol (70%, v/v) in an aqueous solution denatured according to Alcohol and Tobacco Tax and Trade Bureau regulations in 27 CFR part 20.
2. Aloe Barbadensis Leaf
3. Carbomer
4. Dimethicone
5. Triisopropanolamine
6. Water

Active Ingredient(s)

Ethyl Alcohol 70% v/v. Purpose: Antiseptic

Purpose

Antiseptic, Hand Sanitizer

Use

For handwashing to decrease bacteria on the skin.

Warnings

Flammable. Keep away from heat or flame. For external use only.

Do not use in eyes. In case of contact with eyes, rinse with water.

Stop use and ask a doctor if irritation or redness develop and persist.

Keep out of reach of children. If swallowed, get medical help promptly.

Directions

Wet hands thoroughly with product and allow to dry without wiping.

Other information

- Store under 105F

Inactive ingredients

Aloe Barbadensis Leaf, Carbomer, Dimethicone, Triisopropanolamine, Water

Package Label - Principal Display Panel

237ml NDC: 75498-070-08

PACKAGE LABEL

3785ml NDC: 75498-070-01

PACKAGE LABEL

473ml NDC: 75498-070-16